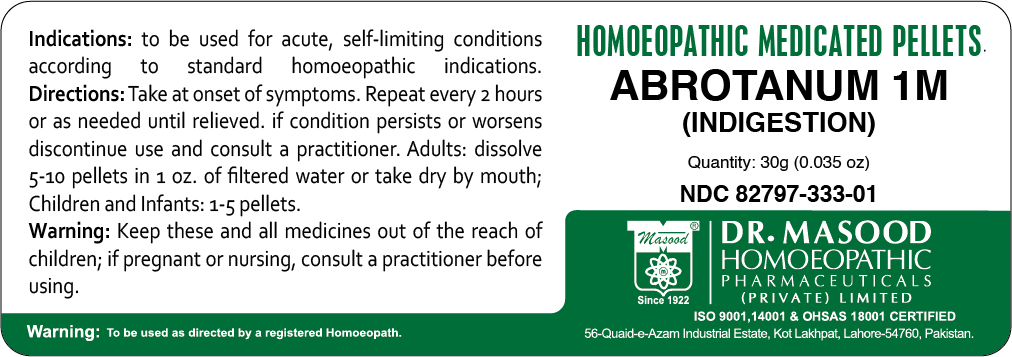 DRUG LABEL: Masood Abrotanum
NDC: 82797-333 | Form: PELLET
Manufacturer: Dr. Masood Homeopathic Pharmaceutical Private Limited
Category: homeopathic | Type: HUMAN OTC DRUG LABEL
Date: 20230113

ACTIVE INGREDIENTS: ARTEMISIA ABROTANUM FLOWERING TOP 1 g/30 g
INACTIVE INGREDIENTS: LACTOSE MONOHYDRATE 9 g/30 g

Masood Abrotanum

Masood Abrotanum

Adults: Dissolve 5-10 pellets in 1 oz. of filtered water or take dry by mouth

Children and Infants: 1-5 pellets

Masood Abrotanum

to be used for acute, self-limiting conditions according to standard hmeopathic indications

Masood Abrotanum

Lactose

Masood Abrotanum

Abrotanum

KEEP OUT OF REACH OF CHILDREN

Keep all medications out of the reach of children

Purpose

WARNINGS

If pregnant or nursing consult a practitioner before using